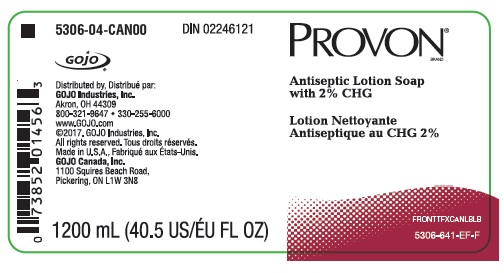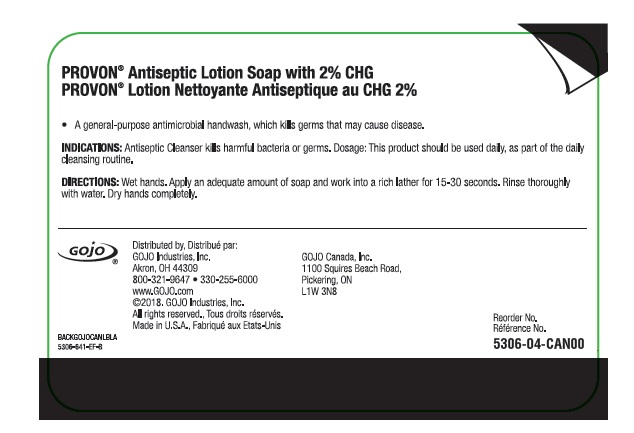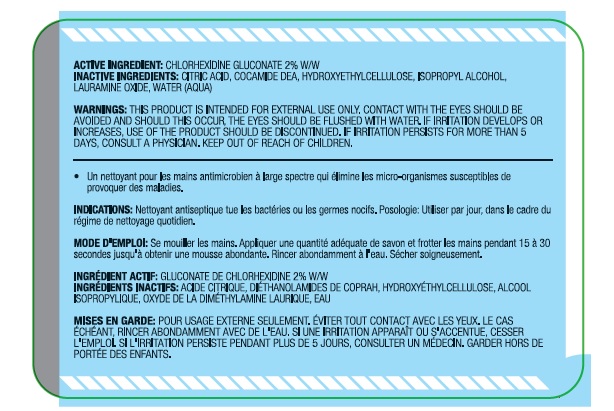 DRUG LABEL: Antiseptic Foam Handwash
NDC: 21749-461 | Form: LIQUID
Manufacturer: GOJO Industries, Inc.
Category: otc | Type: HUMAN OTC DRUG LABEL
Date: 20180824

ACTIVE INGREDIENTS: CHLORHEXIDINE GLUCONATE 20 mg/1 mL
INACTIVE INGREDIENTS: HYDROXYETHYL CELLULOSE (2000 CPS AT 1%); WATER; ISOPROPYL ALCOHOL; COCO DIETHANOLAMIDE; CITRIC ACID MONOHYDRATE; LAURAMINE OXIDE

GOJO Canada

Active Ingredient/ Ingrédient Actif

Chlorhexidine Gluconate 2% W/W

Gluconate De Chlorhexidine 2% W/W

Purpose

A general purpose antimicrobial handwash, which kills germs that may cause disease.

Un nettoyant pour les mains antimicrobien á large spectre qui élimine les micro-organismes susceptibles de provoquer des maladies.

Indications

Antiseptic cleanser kills harmful bacteria or germs. Dosage: This product should be used daily, as part of the daily cleansing routine

Nettoyant antiseptique tue les bactéries ou les germes nocifs. Posologie: Utiliser par jour, dan le cadre du régime de nettoyage quotidien.

Directions/Mode D'emploi

Wet hands. Apply an adequate amount of soap and work into a rich lather for 15-30 seconds. Rinse thoroughly with water. Dry hands completely.

Se mouiller les maines. Appliquer une quantité adéquate de savon et frotter les mains pendant 15 á 30 secondes jusqu á obtenir une mousse abondante. Rincer abondamment á l'eau. Sécher soigneusement.

Warnings/Mises en Garde

This product is intended for external use only. Contact with the eyes should be avoided and should this occur, the eye should be flushed with water. If irritation develops or increases, use of the product should be disontinued. If irritattion persists for moe than 5 days, consult a physician. Keep out of reach of children.

Pour usage externe seulement, éviter tout contact avec les yeux, le cas échéant, rincer abondamment avec de l'eau, si une irritation apparaít ou s'accentue, cesser l'empoli. Si l'irritation persiste pendant plus de 5 jours, consulter un médcin. Garder hors de portée des enfants.

Inactive Ingredients

Citric acid, cocamide DEA, Hydroxyethylcellulose, Isopropyl Alcohol, Lauramine Oxide, Water (Aqua)

Acide citrique, diéthanolamide de coprah, hydroxyéthylcellulose, alcool isopropylique, oxyde de la diméthylamine laurique, Eau

PACKAGE LABEL

NDC 21749-461-89

Chlorhexidine Gluconate 2% Solution

Antiseptic Lotion Soap

Distributed by:

GOJO Industries, Inc.

Akron, OH 44309

330-255-6000

www.GOJO.com

GOJO Canada, Inc.

1100 Squires Beach Road

Pickering, ON L1W 3N8

FRONTTTFXCANLBLB

NDC 21749-461-89

Chlorhexidine Gluconate 2% Solution

Antiseptic Lotion Soap

Distributed by:

GOJO Industries, Inc.

Akron, OH 44309

330-255-6000

www.GOJO.com

GOJO Canada, Inc.

1100 Squires Beach Road

Pickering, ON L1W 3N8

BACKGOJOCANLBLA